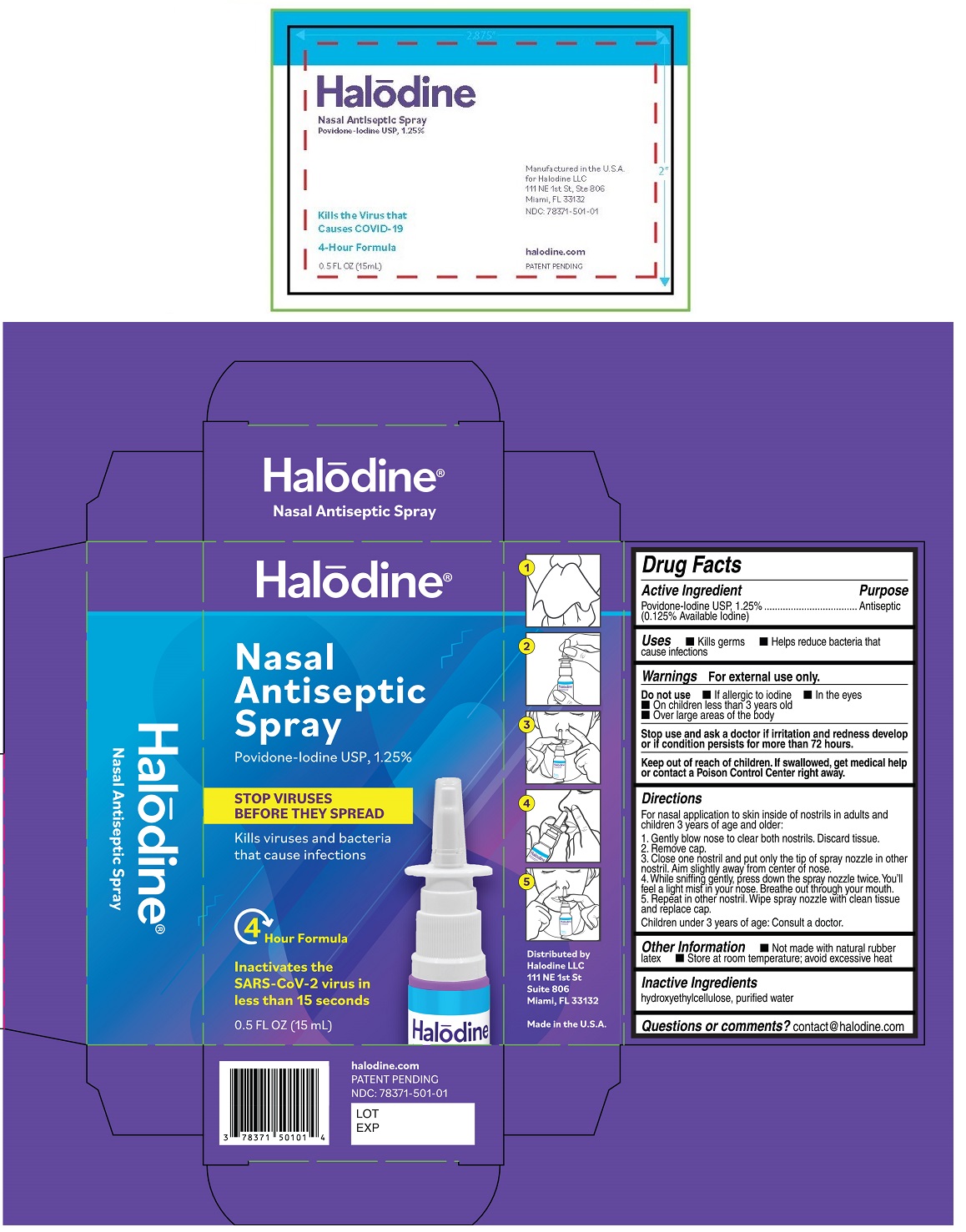 DRUG LABEL: Halodine Nasal Antiseptic
NDC: 78371-501 | Form: SPRAY
Manufacturer: Halodine Llc
Category: otc | Type: HUMAN OTC DRUG LABEL
Date: 20210204

ACTIVE INGREDIENTS: POVIDONE-IODINE 1.25 g/100 mL
INACTIVE INGREDIENTS: HYDROXYETHYL CELLULOSE, UNSPECIFIED; WATER

Halodine® Nasal Antiseptic Spray

Active Ingredient

Povidone-Iodine USP, 1.25%

(0.125% Available Iodine)

Purpose

Antiseptic

Uses

• Kills germs • Helps reduce bacteria that cause infections

Warnings

For external use only.

Do not use • If allergic to iodine • In the eyes

• On children less than 3 years old
• Over large areas of the body

Stop use and ask a doctor if irritation and redness develop or if condition persists for more than 72 hours.

Keep out of reach of children. If swallowed, get medical help or contact a Poison Control Center right away.

Directions

For nasal application to skin inside of nostrils in adults and children 3 years of age and older:

1. Gently blow nose to clear both nostrils. Discard tissue.

2. Remove cap.

3. Close one nostril and put only the tip of spray nozzle in other nostril. Aim slightly away from center of nose.

4. While sniffing gently, press down the spray nozzle twice. You'll feel a light mist in your nose. Breathe out through your mouth.

5. Repeat in other nostril. Wipe spray nozzle with clean tissue and replace cap.

Children under 3 years of age: Consult a doctor.

Other Information

• Not made with natural rubber latex • Store at room temperature; avoid excessive heat

Inactive Ingredients

hydroxyethylcellulose, purified water

Questions or comments?

contact@halodine.com

STOP VIRUSES BEFORE THEY SPREAD

Kills viruses and bacteria that cause infections

Kills the virus that causes COVID-19

4 Hour Formula

Inactivates the SARS-CoV-2 virus in less than 15 seconds

Distributed by

Halodine LLC

111 NE 1st St

Suite 806

Miami, FL 33132

Made in the U.S.A

halodine.com